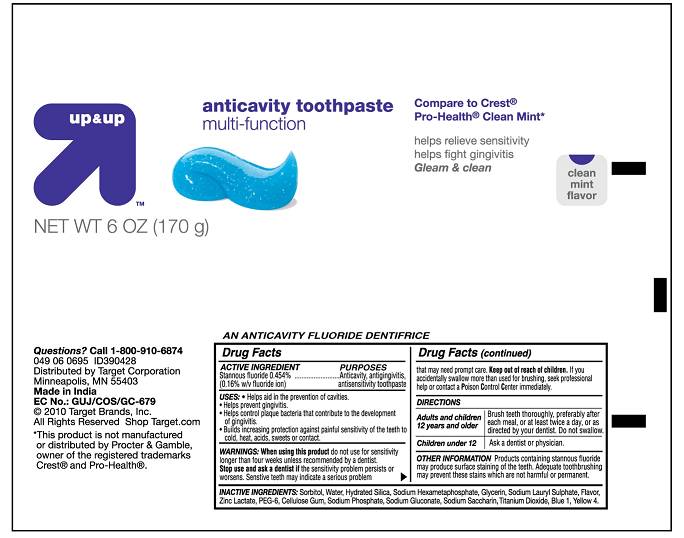 DRUG LABEL: Up and Up Anticavity Toothpaste Multi Function
NDC: 67659-083 | Form: PASTE, DENTIFRICE
Manufacturer: Team Technologies, Inc
Category: otc | Type: HUMAN OTC DRUG LABEL
Date: 20100825

ACTIVE INGREDIENTS: STANNOUS FLUORIDE 4.54 mg/1 g
INACTIVE INGREDIENTS: SORBITOL; WATER; SILICON DIOXIDE; SODIUM POLYMETAPHOSPHATE; GLYCERIN; SODIUM LAURYL SULFATE; ZINC LACTATE; POLYETHYLENE GLYCOL 300; CROSCARMELLOSE SODIUM; SODIUM PHOSPHATE; SODIUM GLUCONATE; SACCHARIN SODIUM; TITANIUM DIOXIDE; FD&C BLUE NO. 1

Up and UP Anticavity Toothpaste Multi-Function

Active Ingredients

STANNOUS FLUORIDE 0.454%...................... ANTICAVITY, ANTIGINGIVITIS,
(0.16% W/V FLUORIDE ION) ANTISENSITIVITY TOOTHPASTE

USES

- HELPS AID IN THE PREVENTION OF CAVITIES
- HELPS PREVENT GINGIVITIS
- HELPS CONTROL PLAQUE BACTERIA THAT CONTRIBUTE TO THE DEVELOPMENT OF GINGIVITIS
- BUILD INCREASING PROTECTION AGAINST PAINFUL SENSITIVITY OF THE TEETH TO COLD, HEAT, ACIDS, SWEETS OR CONTACT.

WARNINGS

WARNINGS: WHEN USING THIS PRODUCT DO NOT USE FOR SENSITIVITY LONGER THAN FOUR WEEKS UNLESS RECOMMENDED BY A DENTIST. STOP USE AND ASK A DENTIST IF THE SENSITIVITY PROBLEM PERSISTS OR WORSENS. SENSITIVE TEETH MAY INDICATE A SERIOUS PROBLEM THAT MAY NEED PROMPT CARE. If you accidentally swallow more than used for brushing, seek professional help or contact a Poison Control Center immediately.

Directions

Adults and children 12 years and older Brush teeth thoroughly, PREFERABLY AFTER EACH MEAL,or at least twice a day, or as directed by your dentist. DO NOT SWALLOW
Children under 12 ASK A dentist or PHYSICIAN
Other information PRODUCTS CONTAINING STANNOUS FLUORIDE MAY PRODUCE SURFACE STAINING OF THE TEETH. ADEQUATE TOOTHBRUSHING MAY PREVENT THESE STAIN WHICH ARE NOT HARMFUL OR PERMANENT.

Inactive ingredients:

Sorbitol, Water, HYDRATED SILICA, SODIUM HEXAMETAPHOSPHATE, Glycerin, SODIUM LAURYL SULPHATE, flavor, ZINC LACTATE, PEG-6, CELLULOSE GUM, SODIUM PHOSPHATE, SODIUM GLUCONATE, Sodium Saccharin, Titanium Dioxide, BLUE 1, YELLOW 4.

PURPOSE

ANTICAVITY, ANTIGINGIVITIS, ANTISENSITIVITY TOOTHPASTE

KEEP OUT OF REACH OF CHILDREN